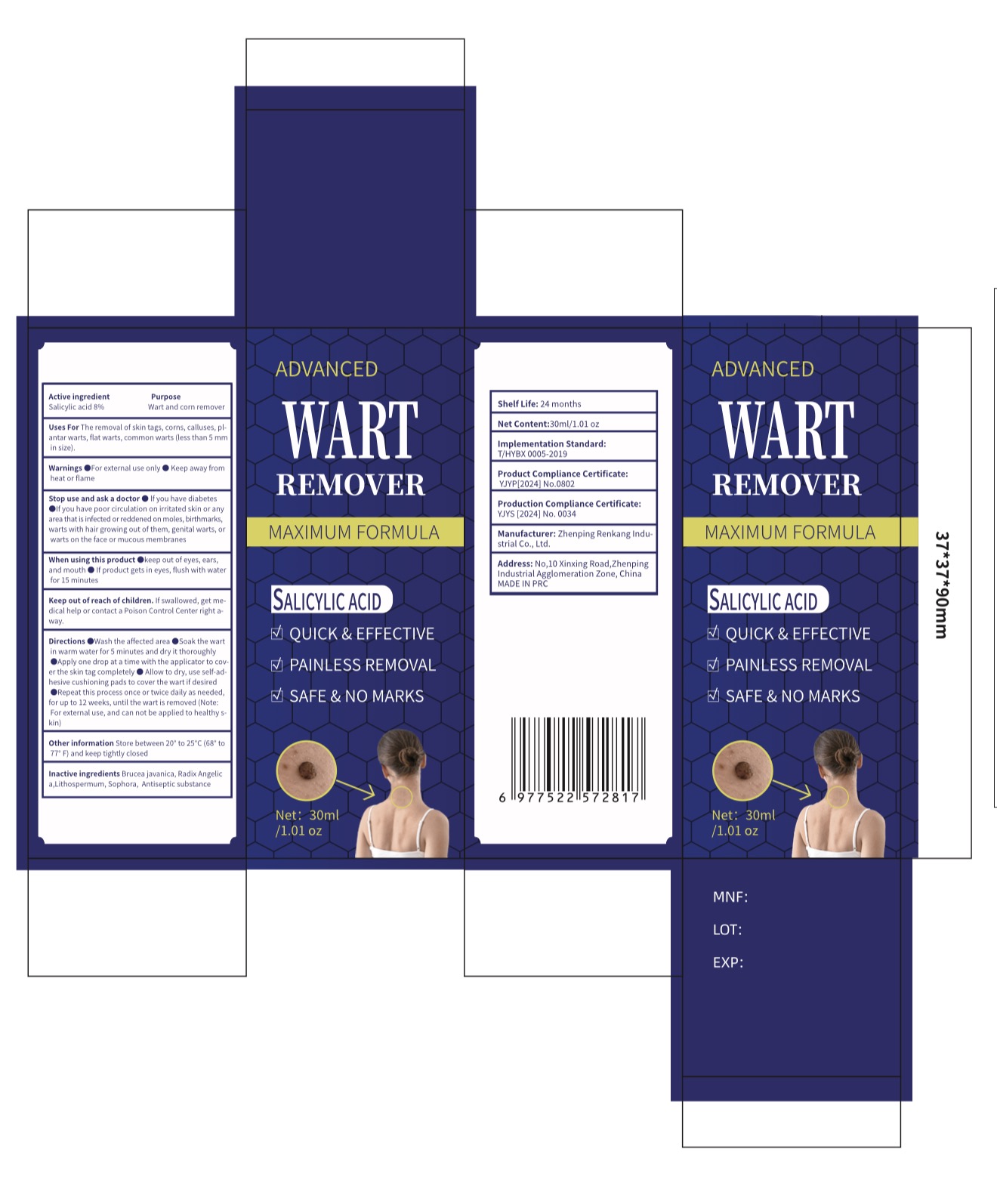 DRUG LABEL: ADVANCED WART REMOVER
NDC: 85593-115 | Form: LIQUID
Manufacturer: Guangzhou ChuanMa International Trading Co.,Ltd.
Category: otc | Type: HUMAN OTC DRUG LABEL
Date: 20251022

ACTIVE INGREDIENTS: SALICYLIC ACID 8 g/100 mL
INACTIVE INGREDIENTS: ANGELICA SINENSIS ROOT; LITHOSPERMUM ERYTHRORHIZON ROOT; BRUCEA JAVANICA WHOLE; SOPHORA FLAVESCENS ROOT

Active ingredientSalicylic acid 896
Purpose
Wart and corn remover

PURPOSE

Uses For The removal of skin tags, corns, calluses, plantar warts, flat warts, common warts (less than 5 mmin size).

WARNINGS

Warnings @For external use only @ Keep away fromheat or flame

Keep out of reach of children, lfswallowed, get me.dical help or contact a Poison Control Center right a-Way.

DOSAGE AND ADMINISTRATION

Directions @Wash the affected area @Soak the wartin warm water for 5 minutes and dry it thoroughlyApply one drop at a time with the applicator to cov.er the skin tag completely @ Allow to dry, use self-ad.hesive cushioning pads to cover the wart if desired@Repeat this process once or twice daily as needed,for up to 12 weeks, until the wart is removed (Note:For externat use, and can not be applied to healthy skin)

INACTIVE INGREDIENT

Inactive ingredients Brucea javanica, Radix Angelica,Lithospermum, Sophora, Antiseptic substance

INDICATIONS AND USAGE

Wash the affected area Soak the wartin warm water for 5 minutes and dry it thoroughly